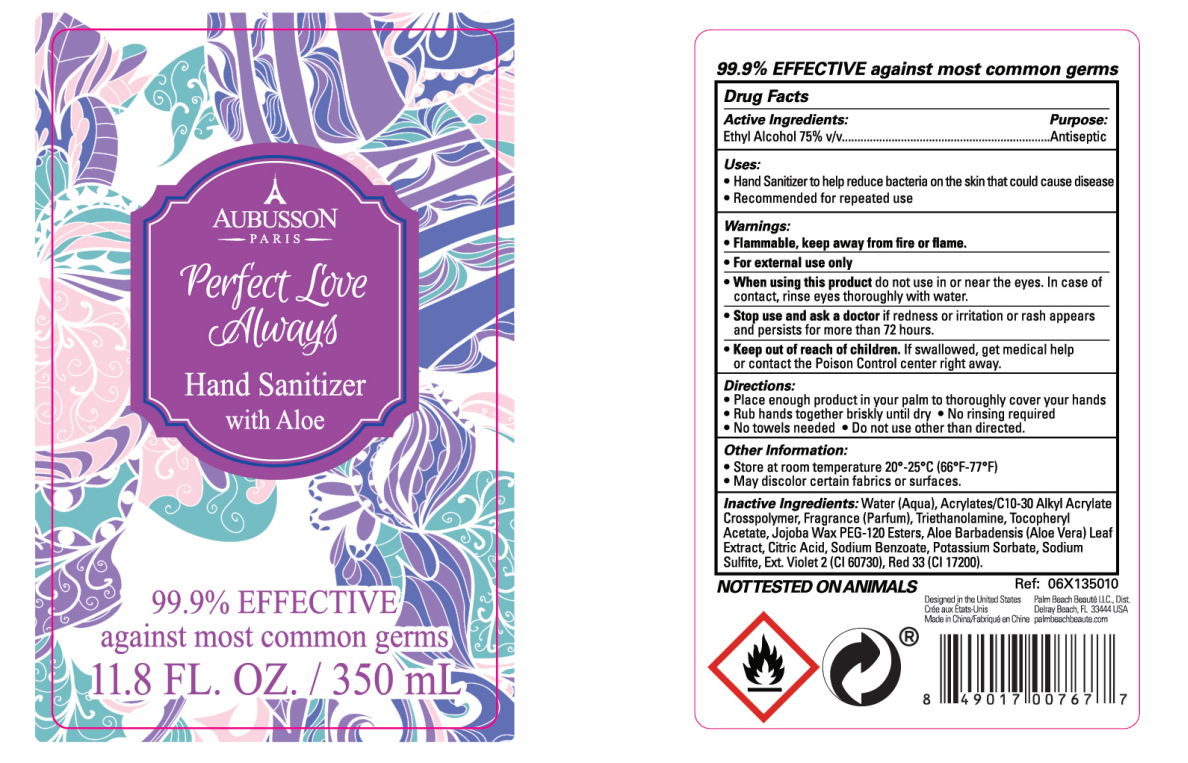 DRUG LABEL: Aubusson Perfect Love Always Hand Sanitizer
NDC: 77218-003 | Form: GEL
Manufacturer: Palm Beach Beaute, LLC
Category: otc | Type: HUMAN OTC DRUG LABEL
Date: 20200426

ACTIVE INGREDIENTS: ALCOHOL 262.5 mL/350 mL
INACTIVE INGREDIENTS: 1-(2,3,8,8-TETRAMETHYL-1,2,3,4,5,6,7,8-OCTAHYDRONAPHTHALEN-2-YL)ETHANONE; METHYL DIHYDROJASMONATE (SYNTHETIC); ETHYLENE BRASSYLATE; CARBOMER COPOLYMER TYPE A (ALLYL PENTAERYTHRITOL CROSSLINKED); SODIUM SULFITE; DIPROPYLENE GLYCOL; D&C RED NO. 33; SODIUM BENZOATE; .ALPHA.-TOCOPHEROL ACETATE; POTASSIUM SORBATE; HEXAMETHYLINDANOPYRAN; WATER; CITRIC ACID MONOHYDRATE; EXT. D&C VIOLET NO. 2; TROLAMINE; ALOE VERA LEAF

DOSAGE AND ADMINISTRATION

Store at room temperature 20*. 25°C (66*F-77*F)

INACTIVE INGREDIENT

Aqua, Acrylates/C10-30 Alkyl Acrylate Crosspolymer, Triethanolamine, Tocopheryl Acetate, Jojoba Wax PEG-120 Esters, Aloe Barbadensis Leaf Extract, Citric Acid, Sodium Benzoate, Potassium Sorbate, Sodium Sulfite, CI 60730, CI 17200, ISO E SUPER, HEDIONE, DIPROPYLENE GLYCOL, GALAXOLIDE, ETHYLENE BRASSILATE.

INDICATIONS AND USAGE

Place enough product in your palm to thoroughly cover your hands Rub hands together briskly until dry.No rinsing required No towels needed.Do not use other than directed.

ACTIVE INGREDIENT

Alcohol

keep out of children

PURPOSE

Disinfection
Sterilization
No Rinseing

WARNINGS

1.Flammable, keep away from fire or fame.
2.For external use only
3.When using this product do not use in or near the eyes. In case of contact, rinse eyes thoroughly with water.
4.Stop use and ask a doctor if redness or iritation or rash appears and persists for more than 72 hours.
5.Keep out of reach of children. If swallowed, get medical help or contact the Poison Control center right away.